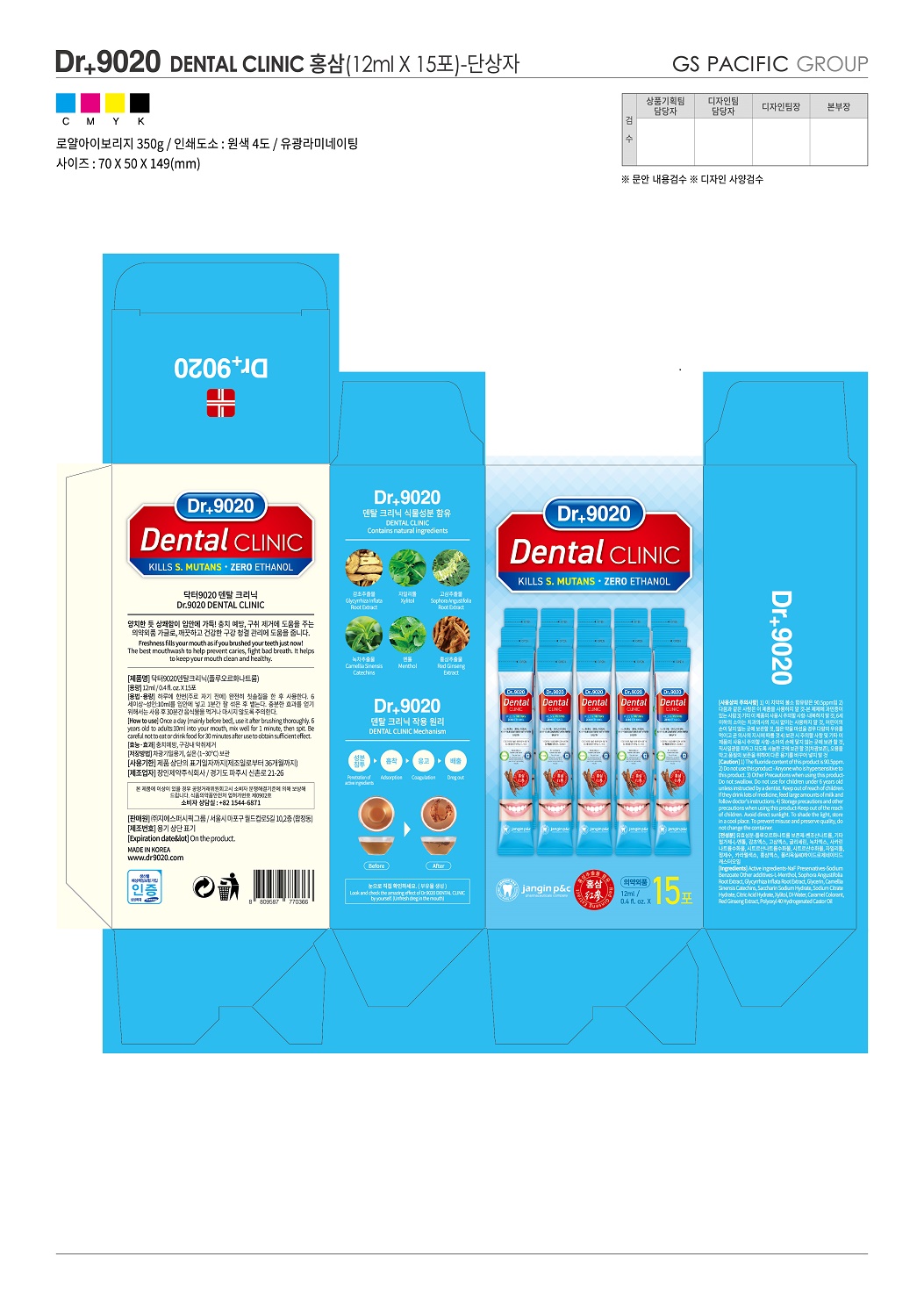 DRUG LABEL: Doctor 9020 Dental Clinic
NDC: 69255-500 | Form: LIQUID
Manufacturer: JANGIN PHARM CO.,LTD.
Category: otc | Type: HUMAN OTC DRUG LABEL
Date: 20191215

ACTIVE INGREDIENTS: SODIUM FLUORIDE 0.02 g/100 mL
INACTIVE INGREDIENTS: XYLITOL; LEVOMENTHOL

Active ingredient : Sodium fluoride

INACTIVE INGREDIENT

Preservatives-Sodium Benzoate

Other additives-L-Menthol, SophoraAngustifolia Root Extract, GlycyrrhizaInflata Root Extract, Glycerin, Camellia SinensisCatechins, Saccharin Sodium Hydrate, Sodium Citrate Hydrate, Citric Acid Hydrate, Xylitol, DI-Water, Caramel Colorant, Red Ginseng Extract, Polyoxyl 40 Hydrogenated Castor Oil

PURPOSE

Effect :prevent cavities, and remove bad breath

Keep out of reach of children

INDICATIONS AND USAGE

Administration and doses : Once a day (mainly before bed), use it after brushing thoroughly. 6 years old to adults:10ml into your mouth, mix well for 1 minute, then spit. Be careful not to eat or drink food for 30 minutes after use to obtain sufficient effect

WARNINGS

●Caution :1) The fluoride content of this product is 90.5ppm. 2) Do not use this product - Anyone who is hypersensitive to this product. 3) Other Precautions when using this product-Do not swallow. Do not use for children under 6 years old unless instructed by a dentist. Keep out of reach of children. If they drink lots of medicine, feed large amounts of milk and follow doctor's instructions. 4) Storage precautions and other precautions when using this product-Keep out of the reach of children. Avoid direct sunlight. To shade the light, store in a cool place. To prevent misuse and preserve quality, do not change the container

DOSAGE AND ADMINISTRATION

For dental use only